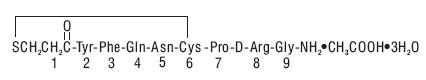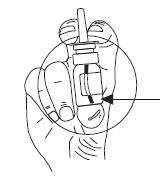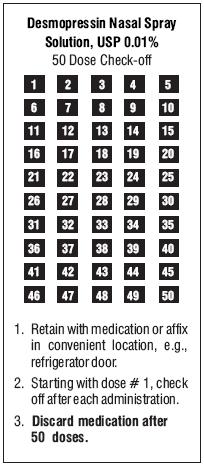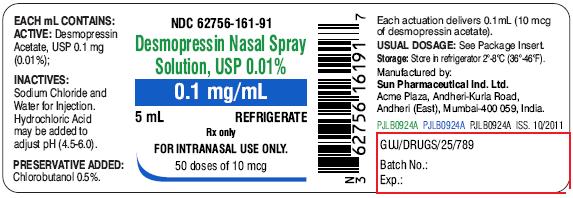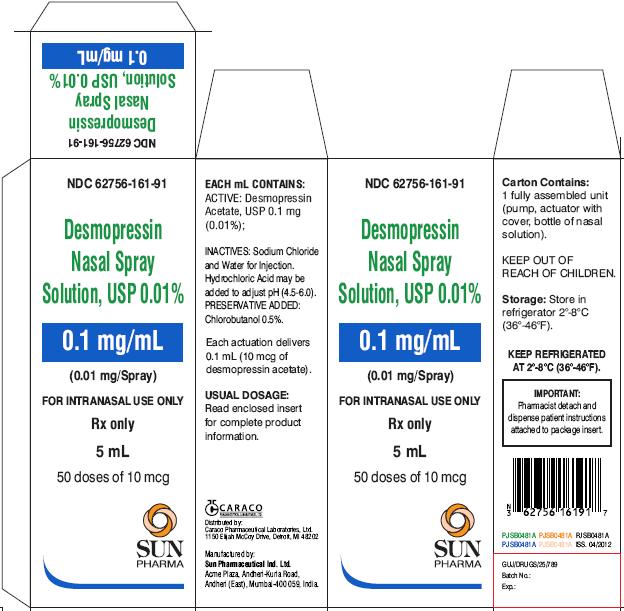 DRUG LABEL: Desmopressin Acetate
NDC: 62756-161 | Form: SOLUTION
Manufacturer: Sun Pharmaceutical Industries, Inc.
Category: prescription | Type: Human Prescription Drug Label
Date: 20181025

ACTIVE INGREDIENTS: DESMOPRESSIN ACETATE 0.1 mg/1 mL
INACTIVE INGREDIENTS: CHLOROBUTANOL HEMIHYDRATE 5.250 mg/1 mL; SODIUM CHLORIDE 9 mg/1 mL; HYDROCHLORIC ACID; WATER

Desmopressin Nasal Spray Solution, USP 0.01%

DESCRIPTION:

Desmopressin nasal spray solution, USP 0.01% is a synthetic analogue of the natural pituitary hormone 8-arginine vasopressin (ADH), an antidiuretic hormone affecting renal water conservation. It is chemically defined as follows:
Mol. Wt. 1183.34
Molecular formula: C46H64N14O12S2•C2H4O2•3H2O

1 - (3-mercaptopropionic acid)-8-D-arginine vasopressin monoacetate (salt) trihydrate.
Desmopressin nasal spray solution, USP 0.01% is provided as an aqueous solution for intranasal use.
Each mL Contains:
Desmopressin Acetate, USP 0.1 mg
Sodium Chloride 9 mg
Hydrochloric Acid may be added to adjust pH (4.5 to 6)
Chlorobutanol (0.5%) 5.25 mg
Water for Injection q.s. to 1 mL
The desmopressin nasal spray solution, USP 0.01% compression pump delivers 0.1 mL (10 mcg) of desmopressin nasal spray solution, USP 0.01% per spray.

CLINICAL PHARMACOLOGY:

Desmopressin acetate is a synthetic analogue of the natural hormone arginine vasopressin. One mL (0.1 mg) of intranasal desmopressin acetate has an antidiuretic activity of about 400 IU; 10 mcg of desmopressin acetate is equivalent to 40 IU.

1. The biphasic half-lives for intranasal desmopressin acetate were 7.8 and 75.5 minutes for the fast and slow phases, compared with 2.5 and 14.5 minutes for lysine vasopressin, another form of the hormone used in this condition. As a result, intranasal desmopressin acetate provides a prompt onset of antidiuretic action with a long duration after each administration.
2. The change in structure of arginine vasopressin to desmopressin acetate has resulted in a decreased vasopressor action and decreased actions on visceral smooth muscle relative to the enhanced antidiuretic activity, so that clinically effective antidiuretic doses are usually below threshold levels for effects on vascular or visceral smooth muscle.
3. Desmopressin acetate administered intranasally has an antidiuretic effect about one-tenth that of an equivalent dose administered by injection.

Human Pharmacokinetics: Desmopressin acetate is mainly excreted in the urine. A pharmacokinetic study conducted in healthy volunteers and patients with mild, moderate, and severe renal impairment (n=24, 6 subjects in each group) receiving single dose desmopressin acetate (2 mcg) injection demonstrated a difference in desmopressin acetate terminal half-life. Terminal half-life significantly increased from 3 hours in normal healthy patients to 9 hours in patients with severe renal impairment. (See CONTRAINDICATIONS.)

INDICATIONS AND USAGE:

Central Cranial Diabetes Insipidus: Desmopressin nasal spray solution, USP 0.01% is indicated as antidiuretic replacement therapy in the management of central cranial diabetes insipidus and for management of the temporary polyuria and polydipsia following head trauma or surgery in the pituitary region. It is ineffective for the treatment of nephrogenic diabetes insipidus.
The use of desmopressin nasal spray solution, USP 0.01% in patients with an established diagnosis will result in a reduction in urinary output with increase in urine osmolality and a decrease in plasma osmolality. This will allow the resumption of a more normal life-style with a decrease in urinary frequency and nocturia.
There are reports of an occasional change in response with time, usually greater than 6 months. Some patients may show a decreased responsiveness, others a shortened duration of effect. There is no evidence this effect is due to the development of binding antibodies but may be due to a local inactivation of the peptide.
Patients are selected for therapy by establishing the diagnosis by means of the water deprivation test, the hypertonic saline infusion test, and/or the response to antidiuretic hormone. Continued response to intranasal desmopressin acetate can be monitored by urine volume and osmolality.
Desmopressin acetate is also available as a solution for injection when the intranasal route may be compromised. These situations include nasal congestion and blockage, nasal discharge, atrophy of nasal mucosa, and severe atrophic rhinitis. Intranasal delivery may also be inappropriate where there is an impaired level of consciousness. In addition, cranial surgical procedures, such as transsphenoidal hypophysectomy create situations where an alternative route of administration is needed as in cases of nasal packing or recovery from surgery.

CONTRAINDICATIONS:

Desmopressin nasal spray solution 0.01% is contraindicated in individuals with known hypersensitivity to desmopressin acetate or to any of the components of desmopressin nasal spray solution 0.01%.
Desmopressin acetate is contraindicated in patients with moderate to severe renal impairment (defined as a creatinine clearance below 50 mL/min).
Desmopressin acetate is contraindicated in patients with hyponatremia or a history of hyponatremia.

WARNINGS:

1. For intranasal use only.
2. Desmopressin nasal spray solution 0.01% should only be used in patients where orally administered formulations are not feasible.
3. Very rare cases of hyponatremia have been reported from world-wide postmarketing experience in patients treated with desmopressin acetate. Desmopressin acetate is a potent antidiuretic which, when administered, may lead to water intoxication and/or hyponatremia. Unless properly diagnosed and treated hyponatremia can be fatal. Therefore, fluid restriction is recommended and should be discussed with the patient and/or guardian. Careful medical supervision is required.
4. When desmopressin nasal spray solution 0.01% is administered, in particular in pediatric and geriatric patients, fluid intake should be adjusted downward in order to decrease the potential occurrence of water intoxication and hyponatremia (See PRECAUTIONS, Pediatric Use and Geriatric Use.) All patients receiving desmopressin nasal spray solution 0.01% therapy should be observed for the following signs or symptoms associated with hyponatremia: headache, nausea/vomiting, decreased serum sodium weight gain, restlessness, fatigue, lethargy, disorientation, depressed reflexes, loss of appetite, irritability, muscle weakness, muscle spasms or cramps and abnormal mental status such as hallucinations, decreased consciousness and confusion. Severe symptoms may include one or a combination of the following: seizure, coma and/or respiratory arrest. Particular attention should be paid to the possibility of the rare occurrence of an extreme decrease in plasma osmolality that may result in seizures which could lead to coma.
5. Desmopressin nasal spray solution 0.01% should be used with caution in patients with habitual or psychogenic polydipsia who may be more likely to drink excessive amounts of water, putting them at greater risk of hyponatremia.

PRECAUTIONS:

General:

Intranasal desmopressin acetate at high dosage has infrequently produced a slight elevation of blood pressure, which disappeared with a reduction in dosage. The drug should be used with caution in patients with coronary artery insufficiency and/or hypertensive cardiovascular disease because of possible rise in blood pressure.
Desmopressin acetate should be used with caution in patients with conditions associated with fluid and electrolyte imbalance, such as cystic fibrosis, heart failure and renal disorders because these patients are prone to hyponatremia.
Rare severe allergic reactions have been reported with desmopressin acetate. Anaphylaxis has been reported rarely with intravenous and intranasal administration of desmopressin acetate.

Central Cranial Diabetes Insipidus:

Since desmopressin acetate is used intranasally, changes in the nasal mucosa such as scarring, edema, or other disease may cause erratic, unreliable absorption in which case intranasal desmopressin acetate should not be used. For such situations, desmopressin acetate injection should be considered.

Information for Patients:

Ensure that in children administration is under adult supervision in order to control the dose intake. Patients should be informed that the desmopressin nasal spray solution 0.01% bottle accurately delivers 50 doses of 10 mcg each. Any solution remaining after 50 doses should be discarded since the amount delivered thereafter may be substantially less than 10 mcg of drug. No attempt should be made to transfer remaining solution to another bottle. Patients should be instructed to read accompanying directions on use of the spray pump carefully before use.
Fluid intake should be adjusted downward based upon discussion with the physician.

Laboratory Tests:

Laboratory tests for following the patient with central cranial diabetes insipidus or post-surgical or head trauma-related polyuria and polydipsia include urine volume and osmolality. In some cases plasma osmolality measurements may be required.

Drug Interactions:

Although the pressor activity of desmopressin acetate is very low compared to the antidiuretic activity, use of large doses of intranasal desmopressin acetate with other pressor agents should only be done with careful patient monitoring. The concomitant administration of drugs that may increase the risk of water intoxication with hyponatremia, (e.g. tricyclic antidepressants, selective serotonin re-uptake inhibitors, chlorpromazine, opiate analgesics, NSAIDs, lamotrigine and carbamazepine) should be performed with caution.

Carcinogenesis, Mutagenesis, Impairment of Fertility:

Studies with desmopressin acetate have not been performed to evaluate carcinogenic potential, mutagenic potential or effects on fertility.

Pregnancy:

Category B: Fertility studies have not been done. Teratology studies in rats and rabbits at doses from 0.05 to 10 mcg/kg/day (approximately 0.1 times the maximum systemic human exposure in rats and up to 38 times the maximum systemic human exposure in rabbits based on surface area, mg/m^2) revealed no harm to the fetus due to desmopressin acetate. There are, however, no adequate and well controlled studies in pregnant women. Because animal reproduction studies are not always predictive of human response, this drug should be used during pregnancy only if clearly needed.
Several publications of desmopressin acetate's use in the management of diabetes insipidus during pregnancy are available; these include a few anecdotal reports of congenital anomalies and low birth weight babies. However, no causal connection between these events and desmopressin acetate has been established. A fifteen year Swedish epidemiologic study of the use of desmopressin acetate in pregnant women with diabetes insipidus found the rate of birth defects to be no greater than that in the general population; however, the statistical power of this study is low. As opposed to preparations containing natural hormones, desmopressin acetate in antidiuretic doses has no uterotonic action and the physician will have to weigh the therapeutic advantages against the possible risks in each case.

Nursing Mothers:

There have been no controlled studies in nursing mothers. A single study in a post-partum woman demonstrated a marked change in plasma, but little if any change in assayable desmopressin acetate in breast milk following an intranasal dose of 10 mcg. It is not known whether this drug is excreted in human milk. Because many drugs are excreted in human milk, caution should be exercised when desmopressin acetate is administered to a nursing woman.

Pediatric Use:

Central Cranial Diabetes Insipidus: Desmopressin nasal spray solution 0.01% has been used in children with diabetes insipidus. Use in infants and children will require careful fluid intake restriction to prevent possible hyponatremia and water intoxication. (See WARNINGS.) The dose must be individually adjusted to the patient with attention in the very young to the danger of an extreme decrease in plasma osmolality with resulting convulsions. Dose should start at 0.05 mL or less.
Since the spray cannot deliver less than 0.1 mL (10 mcg), smaller doses should be administered using the rhinal tube delivery system. Do not use the nasal spray in pediatric patients requiring less than 0.1 mL (10 mcg) per dose.

Geriatric Use:

Clinical studies of desmopressin nasal spray solution 0.01% did not include sufficient numbers of subjects aged 65 and over to determine whether they respond differently from younger subjects. Other reported clinical experience has not identified differences in responses between the elderly and younger subjects. In general, dose selection for an elderly patient should be cautious, usually starting at the low end of the dosing range, reflecting the greater frequency of decreased hepatic, renal, or cardiac function, and of concomitant disease or drug therapy.
This drug is known to be substantially excreted by the kidney, and the risk of toxic reactions to this drug may be greater in patients with impaired renal function. Because elderly patients are more likely to have decreased renal function, care should be taken in dose selection, and it may be useful to monitor renal function. Desmopressin nasal spray solution 0.01% is contraindicated in patients with moderate to severe renal impairment (defined as a creatinine clearance below 50 mL/min). (See CLINICAL PHARMACOLOGY, Human Pharmacokinetics and CONTRAINDICATIONS.)
Use of desmopressin nasal spray solution 0.01% in geriatric patients will require careful fluid intake restriction to prevent possible hyponatremia and water intoxication. (See WARNINGS).
There are reports of an occasional change in response with time, usually greater than 6 months. Some patients may show a decreased responsiveness, others a shortened duration of effect. There is no evidence this effect is due to the development of binding antibodies but may be due to a local inactivation of the peptide.

ADVERSE REACTIONS:

Infrequently, high dosages of intranasal desmopressin acetate have produced transient headache and nausea. Nasal congestion, rhinitis and flushing have also been reported occasionally along with mild abdominal cramps. These symptoms disappeared with reduction in dosage. Nosebleed, sore throat, cough and upper respiratory infections have also been reported.
The following table lists the percentage of patients having adverse experiences without regard to relationship to study drug from the pooled pivotal study data for nocturnal enuresis.

 |  | Desmopressin Acetate
 | PLACEBO (N=59) | 20 mcg (N=60) | 40 mcg (N=61)
ADVERSE REACTION | % | % | %
BODY AS A WHOLE
Abdominal Pain | 0 | 2 | 2
Asthenia | 0 | 0 | 2
Chills | 0 | 0 | 2
Headache | 0 | 2 | 5
NERVOUS SYSTEM
Dizziness | 0 | 0 | 3
RESPIRATORY SYSTEM
Epistaxis | 2 | 3 | 0
Nostril Pain | 0 | 2 | 0
Rhinitis | 2 | 8 | 3
DIGESTIVE SYSTEM
Gastrointestinal Disorder | 0 | 2 | 0
Nausea | 0 | 0 | 2
SPECIAL SENSES
Conjunctivitis | 0 | 2 | 0
Edema Eyes | 0 | 2 | 0
Lachrymation Disorder | 0 | 0 | 2

Post Marketing:

There have been rare reports of hyponatremic convulsions associated with concomitant use with the following medications: oxybutinin and imipramine.
See WARNINGS for the possibility of water intoxication and hyponatremia.

OVERDOSAGE:

Signs of overdose may include confusion, drowsiness, continuing headache, problems with passing urine and rapid weight gain due to fluid retention. (See WARNINGS.) In case of overdosage, the dose should be reduced, frequency of administration decreased, or the drug withdrawn according to the severity of the condition. There is no known specific antidote for desmopressin acetate or desmopressin nasal spray solution 0.01%.
An oral LD50 has not been established. An intravenous dose of 2 mg/kg in mice demonstrated no effect.

DOSAGE AND ADMINISTRATION:

Central Cranial Diabetes Insipidus:

Desmopressin nasal spray solution 0.01% dosage must be determined for each individual patient and adjusted according to the diurnal pattern of response. Response should be estimated by two parameters: adequate duration of sleep and adequate, not excessive, water turnover. Patients with nasal congestion and blockage have often responded well to intranasal desmopressin acetate. The usual dosage range in adults is 0.1 mL to 0.4 mL daily, either as a single dose or divided into two or three doses. Most adults require 0.2 mL daily in two divided doses. The morning and evening doses should be separately adjusted for an adequate diurnal rhythm of water turnover. For children aged 3 months to 12 years, the usual dosage range is 0.05 mL to 0.3 mL daily, either as a single dose or divided into two doses. About 1/4 to 1/3 of patients can be controlled by a single daily dose of desmopressin acetate administered intranasally. Fluid restriction should be observed. (See WARNINGS, PRECAUTIONS, Pediatric Use and Geriatric Use.)
The nasal spray pump can only deliver doses of 0.1 mL (10 mcg) or multiples of 0.1 mL. If doses other than these are required, the rhinal tube delivery system may be used.
The spray pump must be primed prior to the first use. To prime pump, press down five (5) times. The bottle will now deliver 10 mcg of drug per spray. Discard desmopressin nasal spray solution 0.01%

after 50 sprays since the amount delivered thereafter per spray may be substantially less than 10 mcg of drug.

Geriatric Use:

This drug is known to be substantially excreted by the kidney, and the risk of toxic reactions to this drug may be greater in patients with impaired renal function. Because elderly patients are more likely to have decreased renal function, care should be taken in dose selection, and it may be useful to monitor renal function. (See CLINICAL PHARMACOLOGY, Human Pharmacokinetics, CONTRAINDICATIONS, and PRECAUTIONS, Geriatric Use.)

HOW SUPPLIED:

Desmopressin nasal spray solution, USP 0.01% is available in a 5 mL bottle with spray pump delivering 50 sprays of 10 mcg (NDC 62756-161-91).

Storage:

Store in refrigerator at 2°-8°C (36°-46°F).
When traveling, product will maintain stability for up to 3 weeks when stored at room temperature, 22°C (72°F).
STORE BOTTLE IN UPRIGHT POSITION.
Keep out of reach of children
Distributed by:
Caraco Pharmaceutical Laboratories, Ltd.
1150 Elijah McCoy Drive, Detroit, MI 48202
Manufactured by:
Sun Pharmaceutical Industries Ltd.
Acme Plaza, Andheri-Kurla Road,
Andheri (East), Mumbai-400 059, India.
ISS

04/2012
PJPI0203A

PATIENT INSTRUCTION GUIDE

Desmopressin Nasal Spray Solution, USP 0.01%
A better way to deliver desmopressin nasal spray solution, USP 0.01%
Delivering desmopressin nasal spray solution, USP 0.01% more efficiently
Your doctor has prescribed desmopressin nasal spray solution 0.01% as antidiuretic hormone replacement therapy. Follow the dosage schedule that is specified. The convenient nasal spray pump provides an efficient, reliable way to administer your medication. It is important, however, to adhere completely to the following instructions so that you will always receive a consistent dose of your medication.
CAUTION: The nasal spray pump accurately delivers 50 doses of 10 micrograms each. Any

solution remaining after 50 doses should be discarded since the amount delivered thereafter per actuation may be substantially less than 10 micrograms of drug. Do not transfer any remaining solution to another bottle. Please read the following instructions carefully before using the spray pump.
Ensure that in children administration is under adult supervision in order to control the dose intake.
If you accidentally deliver/administer too much of a dose, immediately telephone your doctor or a certified Regional Poison Center for advice. Possible signs of overdose may include confusion, drowsiness, continuing headache, problems with passing urine and rapid weight gain due to fluid retention.
Using your Desmopressin Nasal Spray Solution 0.01% Pump

1. Remove protective cap.

2. The spray pump must be primed prior to the first use. To prime pump, press down five (5) times.

3. Once primed, the spray pump delivers 10 micrograms of medication each time it is pressed. To ensure dosing accuracy, hold bottle upright.

To administer a 10 micrograms dose, place the spray nozzle in nostril and press the spray pump once. If a higher dose has been prescribed, spray half the dose in each nostril. The spray pump cannot be used for doses less than 10 micrograms or doses other than multiples of 10 micrograms.

4. Replace the protective cap on bottle after use, and store in refrigerator. The pump will stay primed for up to one week under refrigeration. If the product has not been used for a period of one week, re-prime the pump by pressing once.

5. We have included a convenient check-off chart to assist you in keeping track of medication doses used. This will help assure that you receive 50 “full doses” of medication. Please note that the bottle has been filled with extra solution to accommodate the initial priming activity.

Storage: Store in refrigerator at 2°-8°C (36°-46°F). When traveling, product will maintain stability for up to 3 weeks when stored at room temperature, 22°C (72°F).
STORE BOTTLE IN UPRIGHT POSITION.
Distributed by:
Caraco Pharmaceutical Laboratories, Ltd.
1150 Elijah McCoy Drive Detroit, MI 48202
Manufactured by:
Sun Pharmaceutical Industries Ltd.
Acme Plaza, Andheri-Kurla Road,
Andheri (East), Mumbai-400 059. India. ISS. 04/2012
PJPI0203A

PACKAGE LABEL.PRINCIPAL DISPLAY PANEL - LABEL

NDC 62756-161-91
Desmopressin Nasal Spray Solution, USP 0.01%
0.1 mg/mL
5 mL
REFRIGERATE
Rx only
FOR INTRANASAL USE ONLY.
50 doses of 10 mcg

PACKAGE LABEL.PRINCIPAL DISPLAY PANEL - CARTON

NDC 62756-161-91
Desmopressin Nasal Spray Solution, USP 0.01%
0.1 mg/mL
(0.01 mg/Spray)
FOR INTRANASAL USE ONLY.
Rx only
5 mL
50 doses of 10 mcg
SUN PHARMA